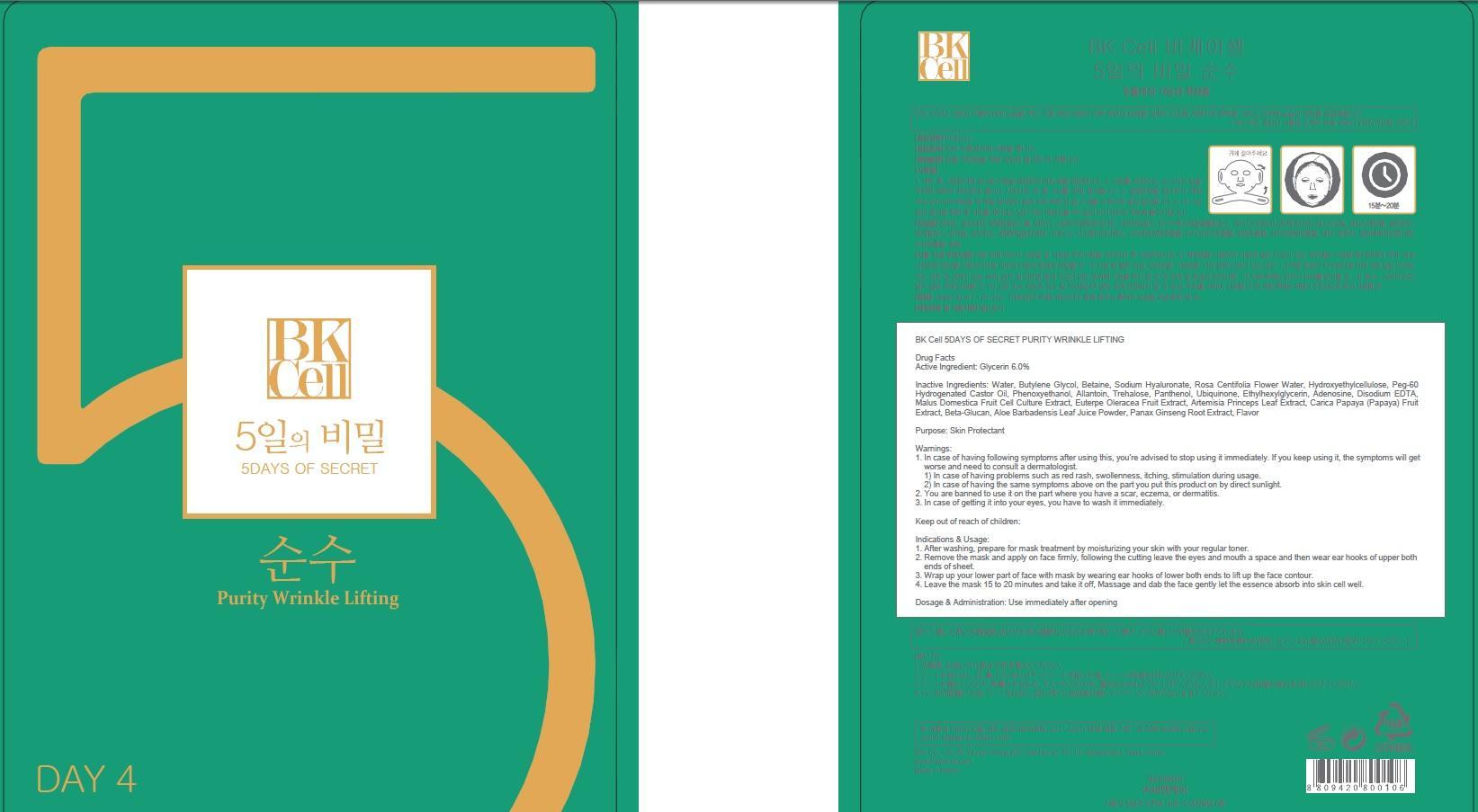 DRUG LABEL: BK Cell 5DAYS OF SECRET PURITY WRINKLE LIFTING
NDC: 69946-040 | Form: PATCH
Manufacturer: BNK CO., LTD.
Category: otc | Type: HUMAN OTC DRUG LABEL
Date: 20150715

ACTIVE INGREDIENTS: Glycerin 1.8 mg/30 mL
INACTIVE INGREDIENTS: Water; Butylene Glycol

ACTIVE INGREDIENT

Active Ingredient: Glycerin 6.0%

INACTIVE INGREDIENT

Inactive Ingredients: Water, Butylene Glycol, Betaine, Sodium Hyaluronate, Rosa Centifolia Flower Water, Hydroxyethylcellulose, Peg-60 Hydrogenated Castor Oil, Phenoxyethanol, Allantoin, Trehalose, Panthenol, Ubiquinone, Ethylhexylglycerin, Adenosine, Disodium EDTA, Malus Domestica Fruit Cell Culture Extract, Euterpe Oleracea Fruit Extract, Artemisia Princeps Leaf Extract, Carica Papaya (Papaya) Fruit Extract, Beta-Glucan, Aloe Barbadensis Leaf Juice Powder, Panax Ginseng Root Extract, Flavor

PURPOSE

Purpose: Skin Protectant

WARNINGS

Warnings: 1. In case of having following symptoms after using this, you're advised to stop using it immediately. If you keep using it, the symptoms will get worse and need to consult a dermatologist. 1) In case of having problems such as red rash, swollenness, itching, stimulation during usage. 2) In case of having the same symptoms above on the part you put this product on by direct sunlight. 2. You are banned to use it on the part where you have a scar, eczema, or dermatitis. 3. In case of getting it into your eyes, you have to wash it immediately.

KEEP OUT OF REACH OF CHILDREN

Keep out of reach of babies and children

INDICATIONS & USAGE

Indications & Usage: 1. After washing, prepare for mask treatment by moisturizing your skin with your regular toner. 2. Remove the mask and apply on face firmly, following the cutting leave the eyes and mouth a space and then wear ear hooks of upper both ends of sheet. 3. Wrap up your lower part of face with mask by wearing ear hooks of lower both ends to lift up the face contour. 4. Leave the mask 15 to 20 minutes and take it off, Massage and dab the face gently let the essence absorb into skin cell well.

DOSAGE & ADMINISTRATION

Dosage & Administration: Use immediately after opening